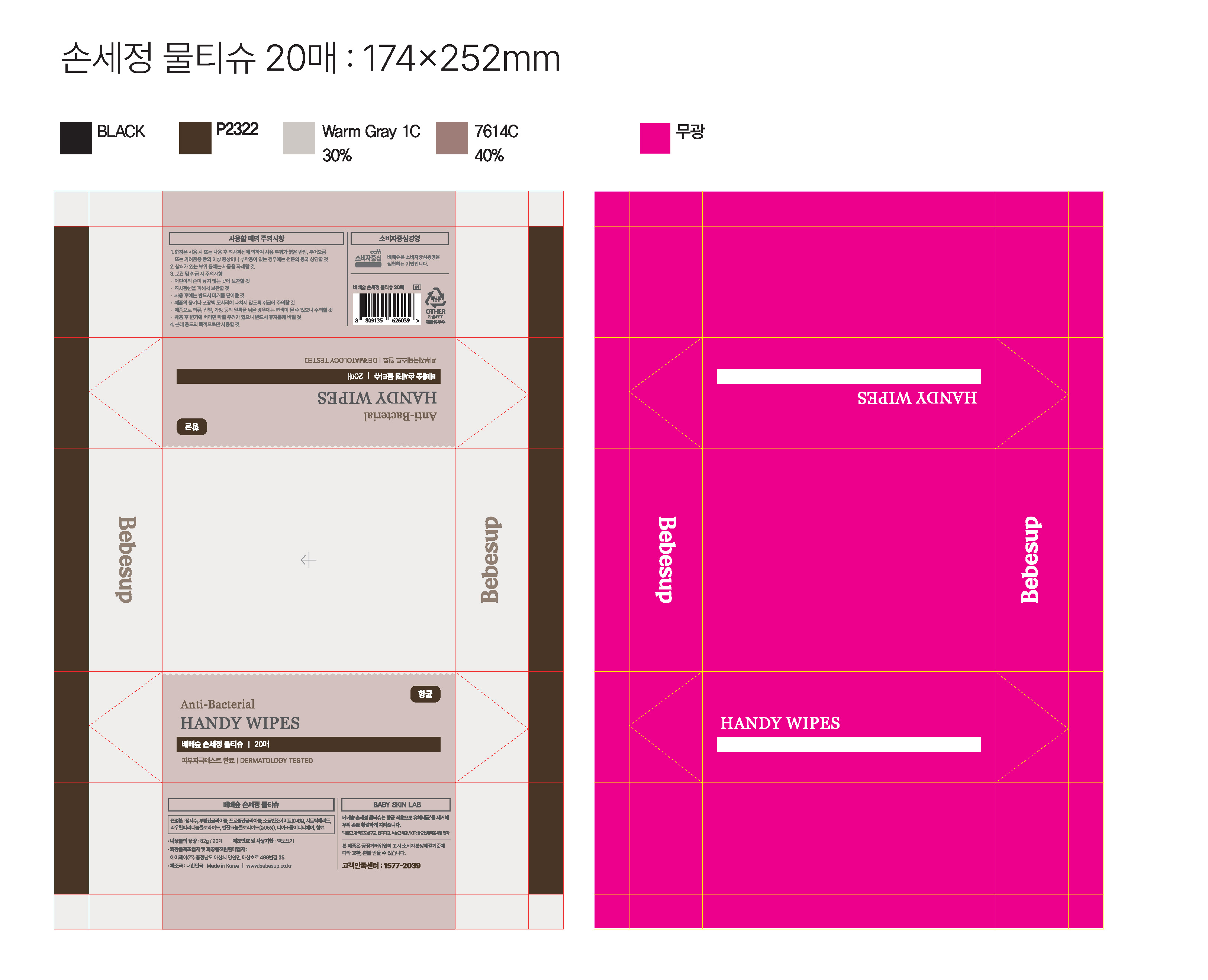 DRUG LABEL: Bebesup Antibacterial Handy Wipes
NDC: 75356-0009 | Form: CLOTH
Manufacturer: AJ Co., Ltd.
Category: otc | Type: HUMAN OTC DRUG LABEL
Date: 20241017

ACTIVE INGREDIENTS: BENZALKONIUM CHLORIDE 0.05 g/100 g
INACTIVE INGREDIENTS: WATER; BUTYLENE GLYCOL

ACTIVE INGREDIENT

Benzalkonium Chloride

INACTIVE INGREDIENT

Water
Butylene Glycol
Propylene Glycol
Sodium Benzoate
Disodium EDTA
Laurylpyridinium Chloride
Citric Acid
Perfume

PURPOSE

It keeps your hands clean by removing harmful germs.

keep out of reach of the children

INDICATIONS AND USAGE

Peel off adhesive flap to pull out wipes. seal back flap to keep wipes moist.

WARNINGS

■ Caution
Do not use as a baby wipe or for personal hygiene.
Use only by hand.
Not flushable.
Discard properly.
For external use only.
Stop using this product if skin irritation occurs.
Avoid contact with eyes and broken skin.
Keep out of reach of children.

DOSAGE AND ADMINISTRATION

Use only on hands